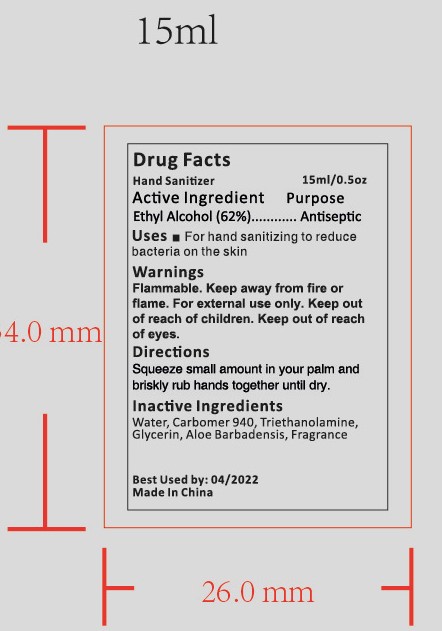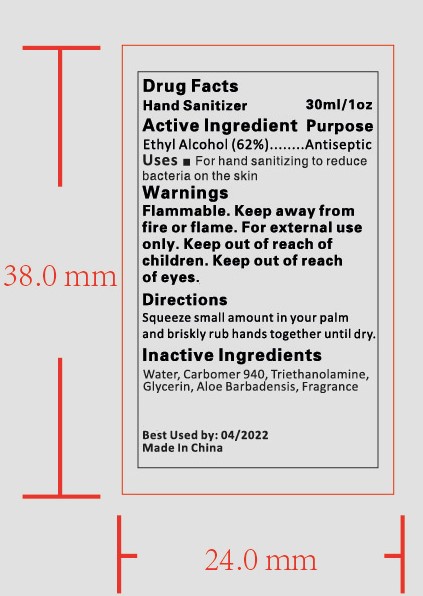 DRUG LABEL: HAND SANITIZER
NDC: 47993-238 | Form: GEL
Manufacturer: NINGBO JIANGBEI OCEAN STAR TRADING CO.,LTD
Category: otc | Type: HUMAN OTC DRUG LABEL
Date: 20201104

ACTIVE INGREDIENTS: ALCOHOL 62 g/112 mL
INACTIVE INGREDIENTS: CARBOMER 940; ALOE VERA LEAF; WATER; TRIETHANOLAMINE BENZOATE; GLYCERIN

47993-238

Active ingredients

Ethyl Alcohol 62%

PURPOSE

Antiseptic

Warnings:

Flammable. Keep away from fire or flame. For external use only. Keep out of reach of children. Keep out of reach of eyes.

Uses：

For hand sanitizing to readuce bacteria on the skin.

Directions:

Squeeze small amounnt in your palm and briskly rub hands together until dry.

Keep out of reach of children.

Inactive Ingredients:

Water,Carbomer 940,Triethanolamine,Glycerin,Aloe Barbadensis,Fragrance